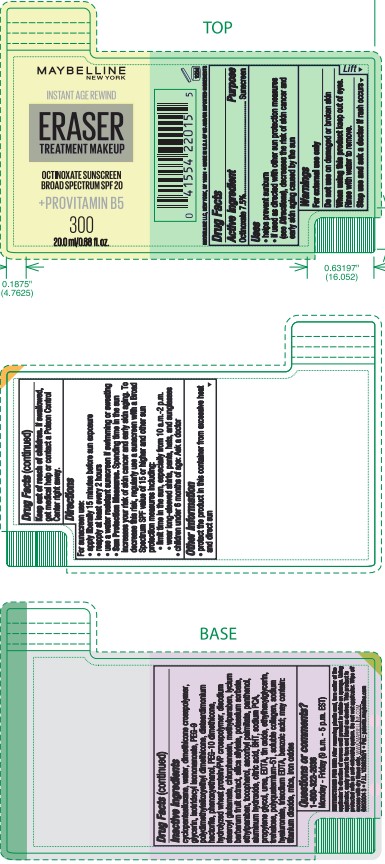 DRUG LABEL: MAYBELLINE NEW YORK INSTANT AGE REWIND ERASER TREATMENT MAKEUP OCTINOXATE BROAD SPECTRUM SPF 20 SUNSCREEN PLUS PROVITAMIN B5
NDC: 49967-202 | Form: LOTION
Manufacturer: L'Oreal USA Products Inc
Category: otc | Type: HUMAN OTC DRUG LABEL
Date: 20240627

ACTIVE INGREDIENTS: Octinoxate 75 mg/1 mL
INACTIVE INGREDIENTS: WATER; GLYCERIN; ISOTRIDECYL ISONONANOATE; PEG-9 POLYDIMETHYLSILOXYETHYL DIMETHICONE; DISTEARDIMONIUM HECTORITE; PHENOXYETHANOL; DISODIUM STEAROYL GLUTAMATE; CHLORPHENESIN; METHYLPARABEN; LYCIUM BARBARUM FRUIT; POTASSIUM SORBATE; ETHYLPARABEN; TOCOPHEROL; ASCORBYL PALMITATE; PANTHENOL; ALUMINUM HYDROXIDE; CITRIC ACID MONOHYDRATE; BUTYLATED HYDROXYTOLUENE; SODIUM PYRROLIDONE CARBOXYLATE; PROPYLENE GLYCOL; UREA; EDETIC ACID; STANNIC OXIDE; ETHYLHEXYLGLYCERIN; TREHALOSE; HYALURONATE SODIUM; EDETATE TRISODIUM; BENZOIC ACID; TITANIUM DIOXIDE; MICA; FERRIC OXIDE RED

Drug Facts

Active ingredient

Octinoxate 7.5%

Purpose

Sunscreen

Uses

- helps prevent sunburn
- if used as directed with other sun protection measures (see Directions), decreases the risk of skin cancer and early skin aging caused by the sun

Warnings

For external use only

Do not use

on damaged or broken skin

When using this product

keep out of eyes. Rinse with water to remove.

Stop use and ask a doctor if

rash occurs

Keep out of reach of children.

If swallowed, get medical help or contact a Poison Control Center right away.

Directions

For sunscreen use:

- apply liberally 15 minutes before sun exposure
- reapply at least every 2 hours
- use a water resistant sunscren if swimming or sweating
- Sun Protection Measures. Spending time in the sun increases our risk of skin cancer and early skin aging. To decrease this risk, regularly use a sunscreen with a Broad Spectrum SPF value of 15 or higher and other sun protection measures including:
- limit time in the sun, especially from 10 a.m. - 2 p.m.
- wear long-sleeved shirts, pants, hats, and sunglasses
- children under 6 months of age: Ask a doctor

Other information

- protect the product in this container from excessive heat and direct sun

Inactive ingredients

cyclopentasiloxane, water, dimethicone crosspolymer, glycerin, isotridecyl isononanoate, PEG-9 polydimethylsiloxyethyl dimethicone, disteardimonium hectorite, phenoxyethanol, PEG-10 dimethicone, hydrolyzed wheat protein/pvp crosspolymer, disodium stearoyl glutamate, chlorphenesin, methylparaben, lycium barbarum fruit extract, silica silylate, potassium sorbate, ethylparaben, tocopherol, ascorbyl palmitate, panthenol, aluminum hydroxide, citric acid, BHT, sodium PCA, propylene glycol, urea, EDTA, tin oxide, ethylhexylglycerin, trehalose, polyquaternium-51, soluble collagen, sodium hyaluronate, trisodium EDTA, benzoic acid; may contain: titanium dioxide, mica, iron oxides

Questions or comments?

1-800-322-2036

Monday - Friday (9 a.m. - 5 p.m. EST)